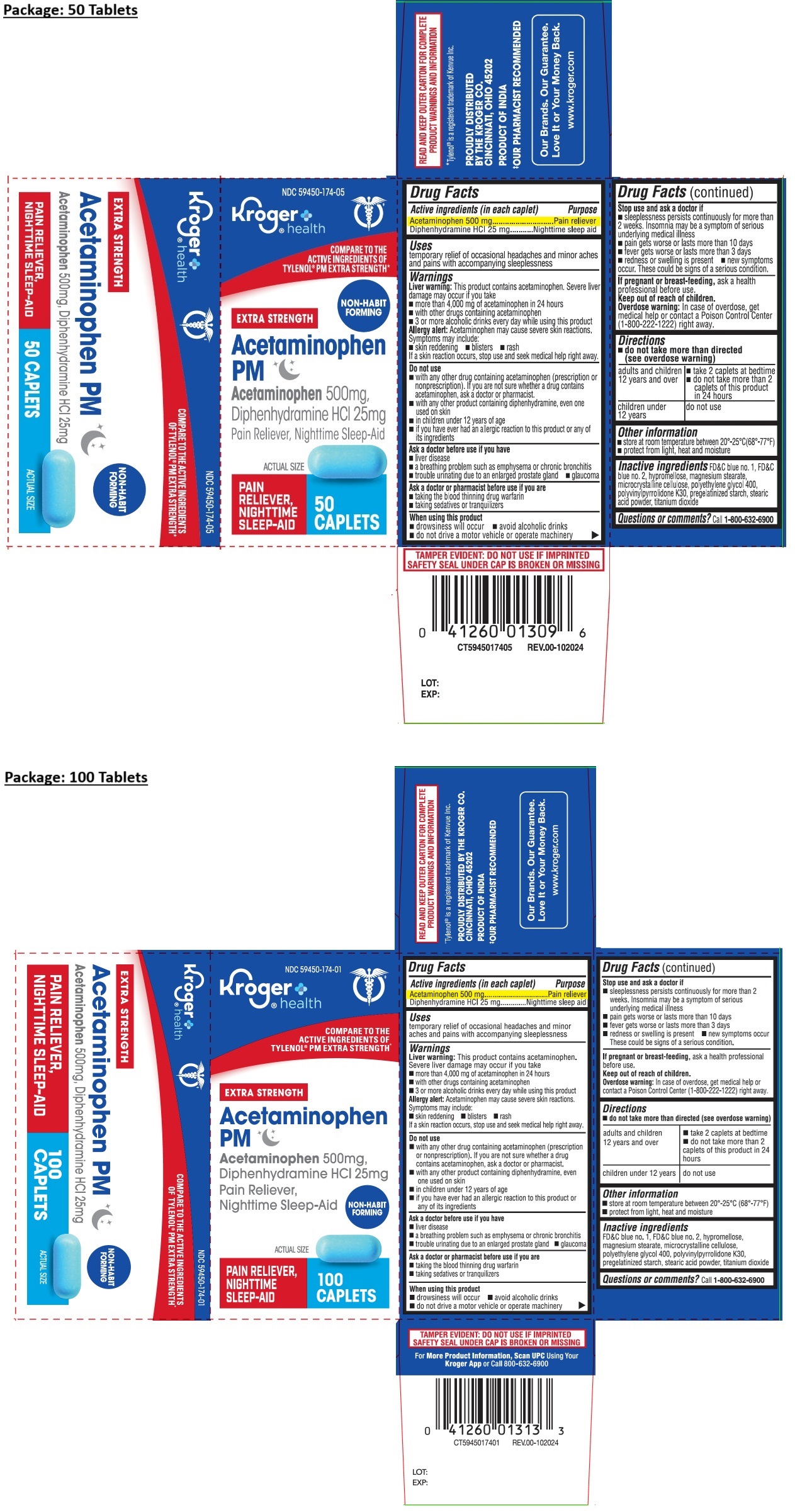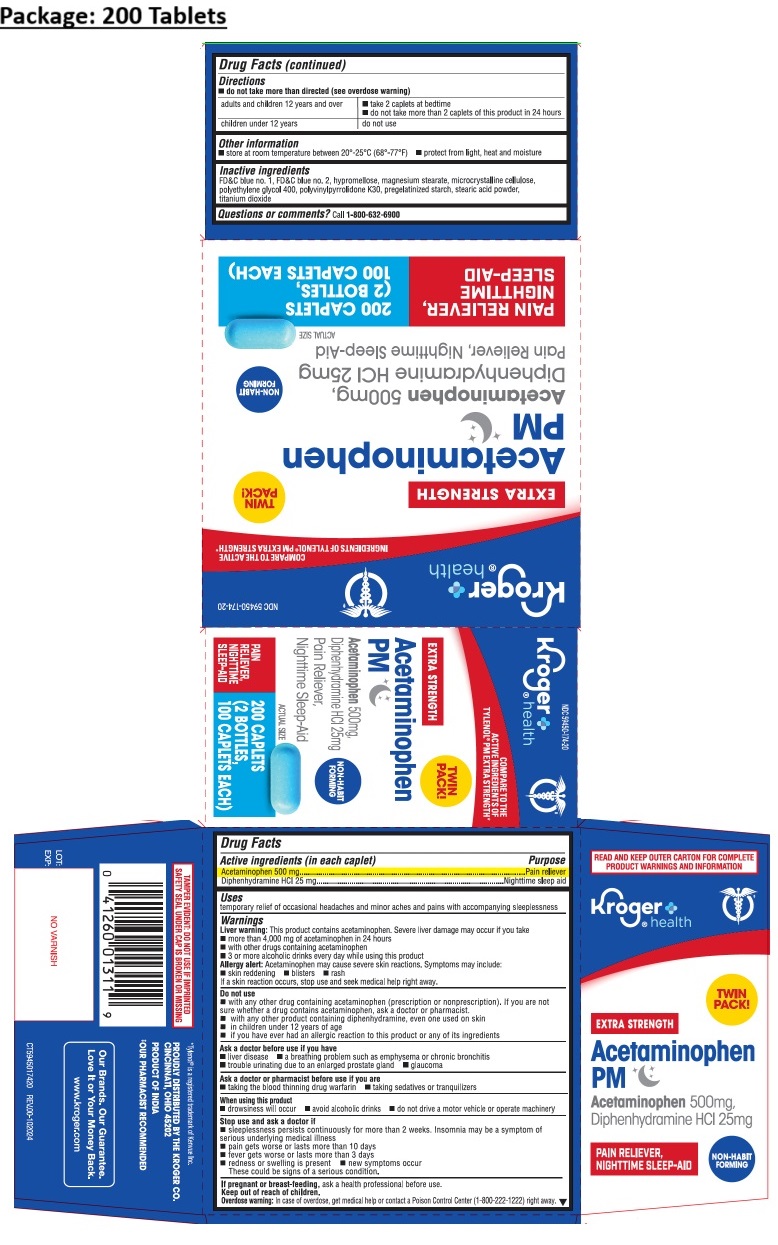 DRUG LABEL: Kroger EXTRA STRENGTH Acetaminophen PM Caplet
NDC: 59450-174 | Form: TABLET
Manufacturer: The Kroger Co.
Category: otc | Type: HUMAN OTC DRUG LABEL
Date: 20241217

ACTIVE INGREDIENTS: ACETAMINOPHEN 500 mg/1 1; DIPHENHYDRAMINE HYDROCHLORIDE 25 mg/1 1
INACTIVE INGREDIENTS: FD&C BLUE NO. 1; FD&C BLUE NO. 2; HYPROMELLOSE, UNSPECIFIED; MAGNESIUM STEARATE; MICROCRYSTALLINE CELLULOSE; POLYETHYLENE GLYCOL 400; POVIDONE K30; STARCH, CORN; STEARIC ACID; TITANIUM DIOXIDE

Kroger EXTRA STRENGTH Acetaminophen PM Caplet

Active ingredients (in each caplet)

Acetaminophen 500 mg
Diphenhydramine HCl 25 mg

Purpose

Pain reliever
Nighttime sleep aid

Uses

temporary relief of occasional headaches and minor aches and pains with accompanying sleeplessness

Warnings

Liver warning: This product contains acetaminophen. Severe liver damage may occur if you take
• more than 4,000 mg of acetaminophen in 24 hours
• with other drugs containing acetaminophen
• 3 or more alcoholic drinks every day while using this product
Allergy alert: Acetaminophen may cause severe skin reactions. Symptoms may include:
• skin reddening • blisters • rash
If a skin reaction occurs, stop use and seek medical help right away.

Do not use
• with any other drug containing acetaminophen (prescription or nonprescription). If you are not sure whether a drug contains acetaminophen, ask a doctor or pharmacist.
• with any other product containing diphenhydramine, even one used on skin
• in children under 12 years of age
• if you have ever had an allergic reaction to this product or any of its ingredients

Ask a doctor before use if you have
• liver disease
• a breathing problem such as emphysema or chronic bronchitis
• trouble urinating due to an enlarged prostate gland • glaucoma

Ask a doctor or pharmacist before use if you are
• taking the blood thinning drug warfarin
• taking sedatives and tranquilizers

When using this product
• drowsiness will occur • avoid alcoholic drinks
• do not drive a motor vehicle or operate machinery

Stop use and ask a doctor if
• sleeplessness persists continuously for more than 2 weeks. Insomnia may be a symptom of a serious underlying medical illness
• pain gets worse or lasts more than 10 days
• fever gets worse or lats more than 3 days.
• redness or swelling is present • new symptoms occur. These could be signs of a serious condition.

If pregnant or breast-feeding, ask a health professional before use.

Keep out of reach of children.
Overdose warning: In case of overdose, get medical help or contact a Poison Control Center (1-800-222-1222) right away.

Directions

do not take more than directed (see overdose warning)

adults and children 12 years and over | • take 2 caplets at bedtime; • do not take more than 2 caplets of this product in 24 hours
children under 12 years | do not use

Other information

• store at room temperature between 20º-25ºC (68º-77ºF)
• protect from light, heat and moisture

Inactive ingredients

FD&C blue no. 1, FD&C blue no. 2, hypromellose, magnesium stearate, microcrystalline cellulose, polyethylene glycol 400, polyvinylpyrrolidone K30, pregelatinized starch, stearic acid powder, titanium dioxide

Questions or comments?

Call 1-800-632-6900

Kroger® health

COMPARE TO THE ACTIVE INGREDIENTS OF TYLENOL® PM EXTRA STRENGTH*

NON-HABIT FORMING

READ AND KEEP OUTER CARTON FOR COMPLETE PRODUCT WARNINGS AND INFORMATION

*Tylenol® is a registered trademark of Kenvue Inc.

PROUDLY DISTRIBUTED BY THE KROGER CO.
CINCINNATI, OHIO 45202

PRODUCT OF INDIA

#OUR PHARMACIST RECOMMENDED

Our Brands. Our Guarantee. Love It or Your Money Back.

www.kroger.com

TAMPER EVIDENT: DO NOT USE IF IMPRINTED SAFETY SEAL UNDER CAP IS BROKEN OR MISSING

For More Product Information, Scan UPC Using Your Kroger App or Call 800-632-6900